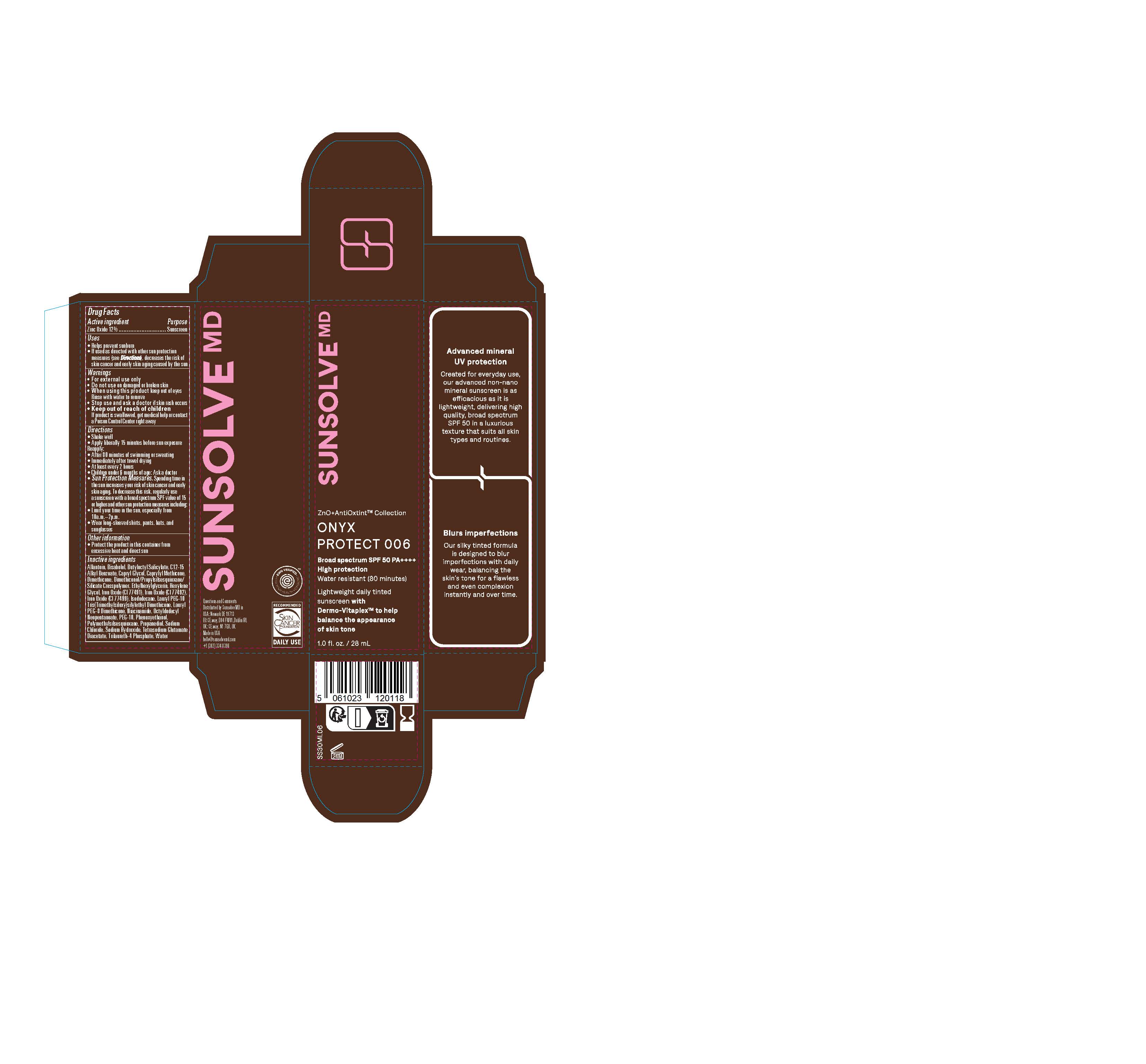 DRUG LABEL: Sunsolve MD Mineral Shade Onyx 006
NDC: 84878-406 | Form: LOTION
Manufacturer: Sunsolve MD Inc
Category: otc | Type: HUMAN OTC DRUG LABEL
Date: 20251114

ACTIVE INGREDIENTS: ZINC OXIDE 132 mg/1 mL
INACTIVE INGREDIENTS: CAPRYLYL METHICONE; LAURYL PEG-8 DIMETHICONE (300 CPS); ALLANTOIN; TRILAURETH-4 PHOSPHATE; FERRIC OXIDE RED; FERRIC OXIDE YELLOW; FERROSOFERRIC OXIDE; CAPRYLYL GLYCOL; PEG-10; BUTYLOCTYL SALICYLATE; OCTYLDODECYL NEOPENTANOATE; ISODODECANE; .ALPHA.-BISABOLOL, (+)-; SODIUM HYDROXIDE; WATER; NIACINAMIDE; ETHYLHEXYLGLYCERIN; HEXYLENE GLYCOL; DIMETHICONOL/PROPYLSILSESQUIOXANE/SILICATE CROSSPOLYMER (450000000 MW); PROPANEDIOL; TETRASODIUM GLUTAMATE DIACETATE; SODIUM CHLORIDE; PHENOXYETHANOL; ALKYL (C12-15) BENZOATE; POLYMETHYLSILSESQUIOXANE (4.5 MICRONS); DIMETHICONE

Sunsolve MD Mineral Shade Onyx 006